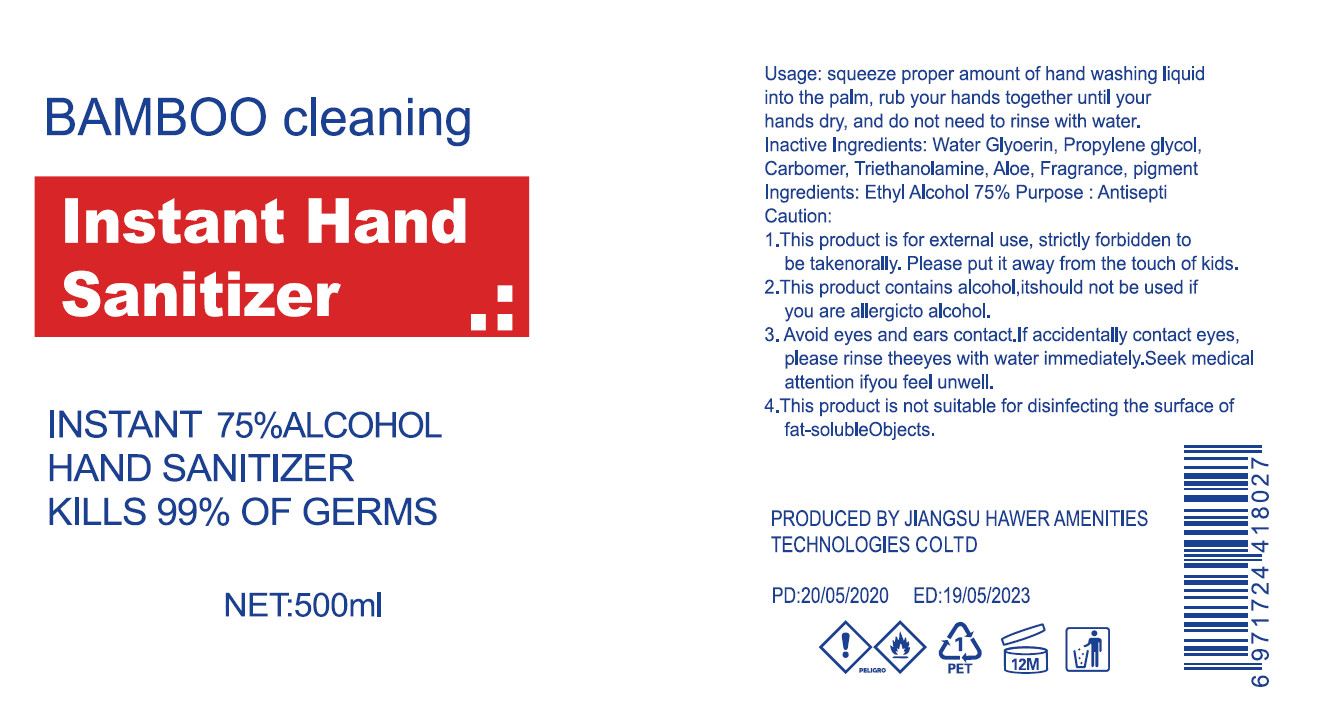 DRUG LABEL: Instant Hand Sanitizer
NDC: 41254-006 | Form: GEL
Manufacturer: Jiangsu Hawer Amenities Technology Co.,Ltd
Category: otc | Type: HUMAN OTC DRUG LABEL
Date: 20200526

ACTIVE INGREDIENTS: ALCOHOL 380 mL/500 mL
INACTIVE INGREDIENTS: CARBOMER HOMOPOLYMER, UNSPECIFIED TYPE; WATER; GLYCERIN; AMINOMETHYLPROPANOL

DOSAGE AND ADMINISTRATION

Store in a cool and dry place

INACTIVE INGREDIENT

Aqua

Glycerin

Carbomer

Aminomethyl Propanol

INDICATIONS AND USAGE

squeeze proper amount of hand washing liquid into the palm, rub your hands together until your hands dry, and do not need to rinse with water.

ACTIVE INGREDIENT

Ethyl Alcohol

keep out of reach of children

PURPOSE

Disinfection
Sterilization
No Rinseing

WARNINGS

1.This product is for external use, strictly forbidden to be takenorally, Please put it away from the touch of kids.
2.This product contains alcohol,itshould not be used if you are allergicto alcohol.
3. Avoid eyes and ears contact.If accidentally contact eyes,please rinse theeyes with water immediately.Seek medical attention ifyou feel unwell.
4.This product is not suitable for disinfecting the surface of fat- solubleObjects.